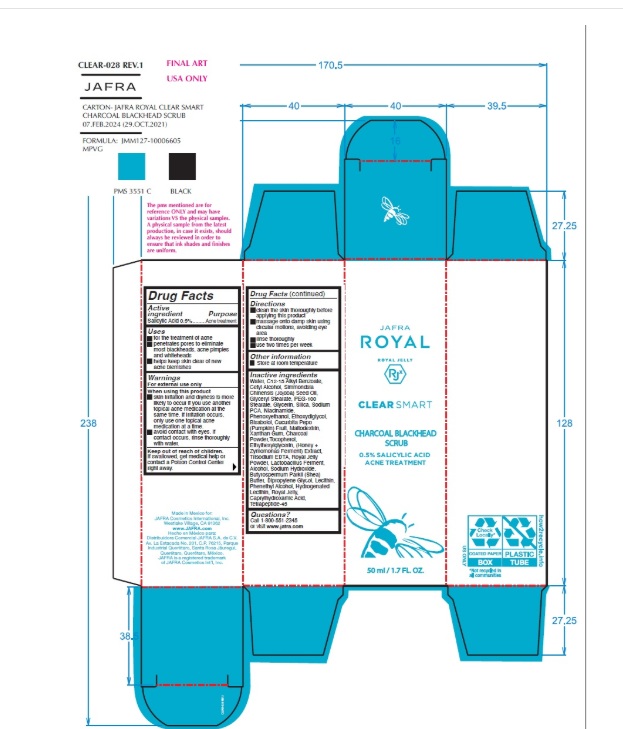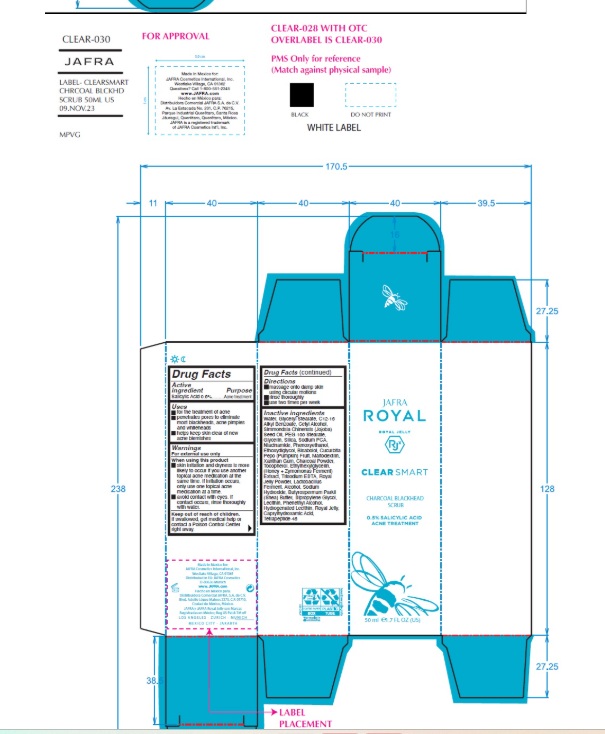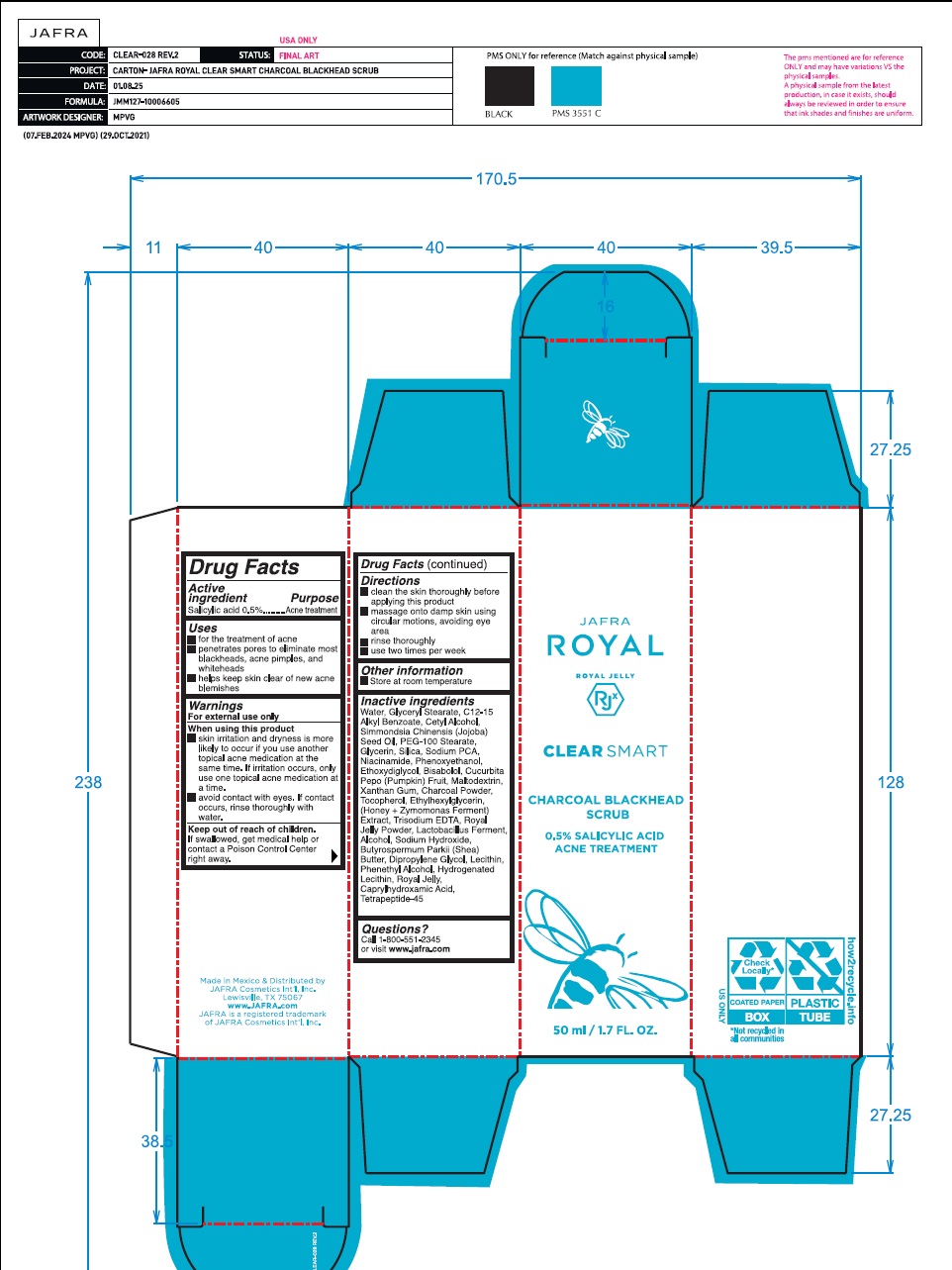 DRUG LABEL: Clear Smart Charcoal Blackhead Scrub
NDC: 68828-001 | Form: CREAM
Manufacturer: Distribuidora Comercial Jafra, S.A. de C.V.
Category: otc | Type: HUMAN OTC DRUG LABEL
Date: 20251105

ACTIVE INGREDIENTS: SALICYLIC ACID 0.5 g/100 mL
INACTIVE INGREDIENTS: LEVOMENOL; PUMPKIN; MALTODEXTRIN; XANTHAN GUM; ACTIVATED CHARCOAL; TOCOPHEROL; ETHYLHEXYLGLYCERIN; EDETATE TRISODIUM; LIMOSILACTOBACILLUS FERMENTUM; ALCOHOL; SODIUM HYDROXIDE; SHEA BUTTER; DIPROPYLENE GLYCOL; LECITHIN, SOYBEAN; PHENYLETHYL ALCOHOL; HYDROGENATED SOYBEAN LECITHIN; ROYAL JELLY; CAPRYLHYDROXAMIC ACID; HONEY; WATER; GLYCERYL MONOSTEARATE; ALKYL (C12-15) BENZOATE; CETYL ALCOHOL; JOJOBA OIL; PEG-100 STEARATE; GLYCERIN; SILICON DIOXIDE; SODIUM PYRROLIDONE CARBOXYLATE; NIACINAMIDE; PHENOXYETHANOL; DIETHYLENE GLYCOL MONOETHYL ETHER

Active ingredient

Salicylic Acid 0.5%

Purpose

Acne treatment

Uses

- For the treatment of acne

- Penetrates pores to eliminate most blackheads, acne pimples and whiteheads

- Helps keep skin clear of new acne blemishes

Warnings

For external use only
When using this product

- skin irritation and dryness is more likely to occur if you use another topical acne medication at the same time. If irritation occurs, only use one topical acne medication at a time.
- avoid contact with eyes. If contact occurs, rinse thoroughly with water.

Keep out of reach of children. If swallowed, get medical help or contact a Poison Control Center right away.

Directions

- Clean the skin thoroughly before applying this product
- Massage onto damp skin using circular motions, avoiding eye area
- Rinse thoroughly
- Use two times per week

Other information

- Store at room temperature

Inactive ingredients

Water, Glyceryl Stearate, C12-15 Alkyl Benzoate, Cetyl Alcohol, Simmondsia Chinensis (Jojoba) Seed Oil, PEG-100 Stearate, Glycerin, Silica, Sodium PCA, Niacinamide, Phenoxyethanol, Ethoxydiglycol, Bisabolol, Cucurbita Pepo (Pumpkin) Fruit, Maltodextrin, Xanthan Gum, Charcoal Powder, Tocopherol, Ethylhexylglycerin, (Honey + Zymomonas Ferment) Extract, Trisodium EDTA, Royal Jelly Powder, Lactobacillus Ferment, Alcohol, Sodium Hydroxide, Butyrospermum Parkii (Shea) Butter, Dipropylene Glycol, Lecithin, Phenethyl Alcohol, Hydrogenated Lecithin, Royal Jelly, Caprylhydroxamic Acid, Tetrapeptide-45

Questions?Call 1-800-551-2345 or visit www.jafra.com